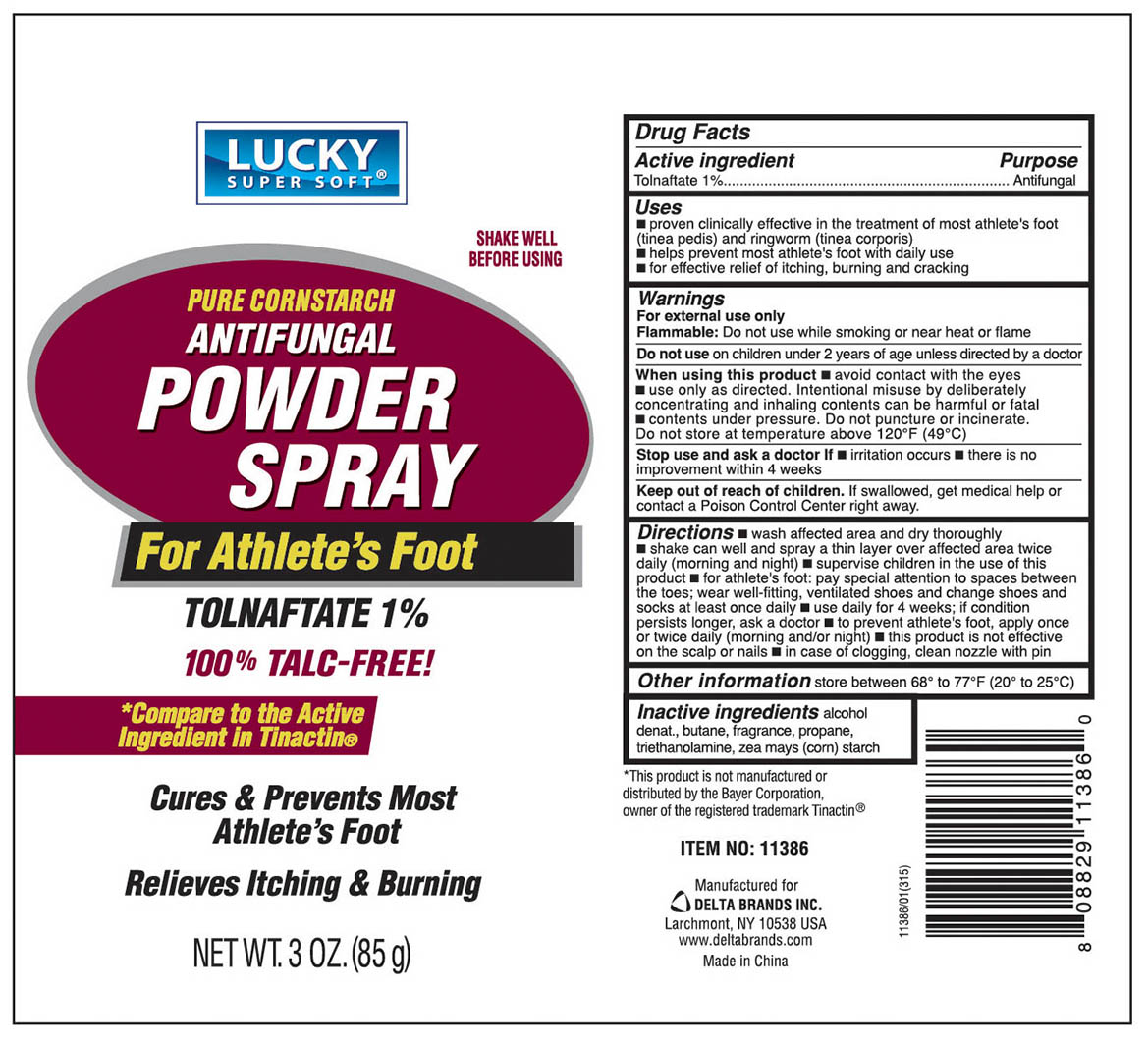 DRUG LABEL: ANTIFUNGAL
NDC: 72109-001 | Form: POWDER
Manufacturer: Dong Yuan Technology Co., Ltd.
Category: otc | Type: HUMAN OTC DRUG LABEL
Date: 20220117

ACTIVE INGREDIENTS: TOLNAFTATE 1 g/100 g
INACTIVE INGREDIENTS: ALCOHOL; BUTANE; PROPANE; TROLAMINE; STARCH, CORN

Antifungal Powder Spray

Active Ingredient

Tolnaftate 1%

Purpose

Antifungal

Uses

■ proven clinically effective in the treatment of most athlete's foot (tinea pedis) and ringworm (tinea corporis) ■ helps prevent most athlete's foot with daily use ■ for effective relief of itching, burning, and cracking

Warnings

For external use only

Flammable: Do not use while smoking or near heat or flame

Do not use

on children under 2 years of age unless directed by a doctor

When using this product

■ avoid contact with eyes ■ use only as directed. Intentional misuse by deliberetely concentrating and inhaling contents can be harmful or fatal ■ contents under pressure. Do not puncture or incinerate.

Do not stire at a temperature above 120ºF (49ºC)

Stop use and ask a doctor if

■ irritation occurs ■ there is no improvement within 4 weeks

Keep out of reach of children

If swallowed, get medical help or contact a Poison Control Center right away

Directions

■ wash affected area and dry thoroughly ■ shake can well and spray a thin layer over affected area twice daily (morning and night) ■ supervise children in the use of this product ■ for athlete's foot, pay special attention to spaces between the toes, wear well-fitting, ventilated shoes and change shoes and socks at least once a day ■ use daily for 4 weeks, if conditions persist longer, ask a doctor ■ to prevent athlete's foot, apply once or twice daily (morning and/or night) ■ this product is not effective on the scalp or nails ■ in case of clogging, clean nozzle with pin

Other information

■ store between 68º to 77ºF (20º to 25ºC)

Inactive ingredients

alcohol denat., butane, fragrance, propane, triethanolamine, zea mays (corn) starch